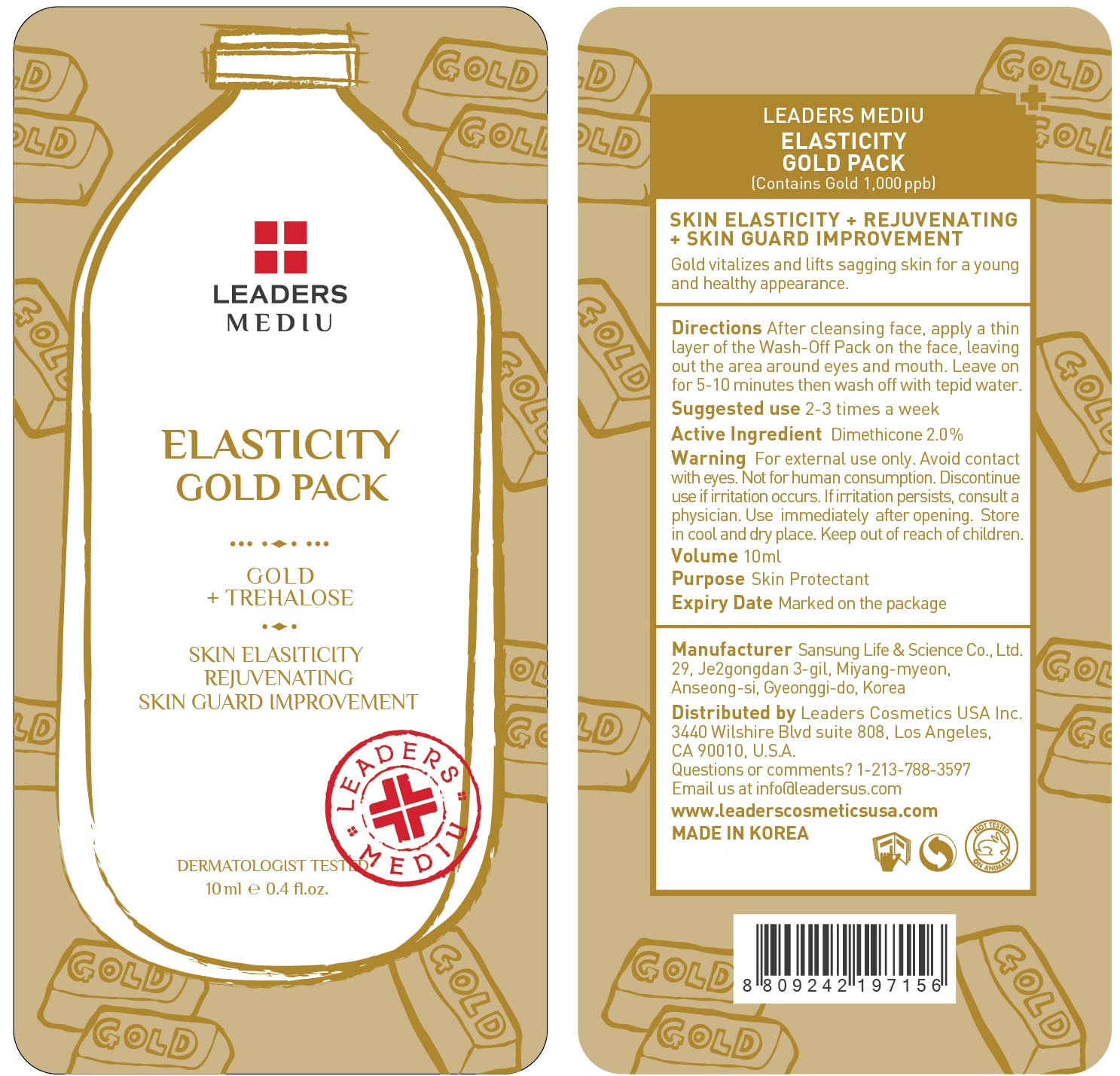 DRUG LABEL: Leaders Mediu Elasticity Gold Pack
NDC: 69424-470 | Form: GEL
Manufacturer: SANSUNG LIFE & SCIENCE CO., LTD.
Category: otc | Type: HUMAN OTC DRUG LABEL
Date: 20160201

ACTIVE INGREDIENTS: Dimethicone 0.2 g/10 mL
INACTIVE INGREDIENTS: Water; Glycerin

ACTIVE INGREDIENT

Active Ingredient: Dimethicone 2.0%

INACTIVE INGREDIENT

Inactive Ingredients: Water, Glycerin, Cetyl Ethylhexanoate, Butylene Glycol, Glyceryl Stearate, Polysorbate 60, Mica, PEG-100 Stearate, Titanium Dioxide, Iron Oxides, Gold, Zanthoxylum Piperitum fruit extract, Pulsatilla koreana extract, Usnea barbata (lichen) extract, Hydroxyethyl Acrylate/Sodium Acryloyldimethyl Taurate Copolymer, Trehalose, Betaine, Carbomer, Tromethamine, Fragrance, PVP, Sodium Citrate, Disodium EDTA

PURPOSE

Purpose: Skin Protectant

WARNINGS

Warnings: For external use only. Avoid contact with eyes. Not for human consumption. Discontinue use if irritation occurs. If irritation persists, consult a physician.

Use immediately after opening. Store in cool and dry place. Keep out of reach of children.

KEEP OUT OF REACH OF CHILDREN

Directions

Directions: After cleansing face, apply a thin layer of the Wash-Off Pack on the face, leaving out the area around eyes and mouth. Leave on for 5-10 minutes then wash off with tepid water. *Suggested use is 2-3 times a week.

Directions

Directions: After cleansing face, apply a thin layer of the Wash-Off Pack on the face, leaving out the area around eyes and mouth. Leave on for 5-10 minutes then wash off with tepid water. *Suggested use is 2-3 times a week.